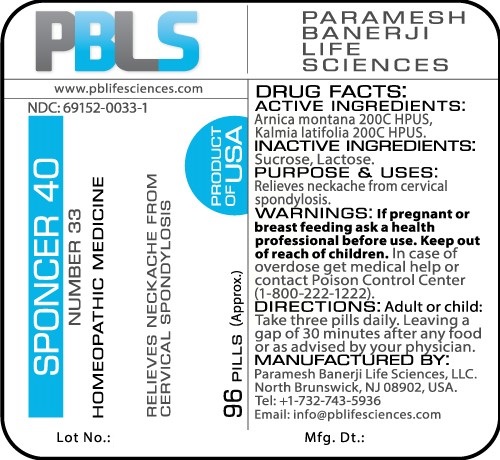 DRUG LABEL: Sponcer 40 (Number 33)
NDC: 69152-0033 | Form: PELLET
Manufacturer: Paramesh Banerji Life Sciences LLC
Category: homeopathic | Type: HUMAN OTC DRUG LABEL
Date: 20161111

ACTIVE INGREDIENTS: ARNICA MONTANA 200 [hp_C]/1 1; KALMIA LATIFOLIA LEAF 200 [hp_C]/1 1
INACTIVE INGREDIENTS: SUCROSE; LACTOSE

DRUG FACTS: Active Ingredients

Arnica montana 200C HPUS, Kalmia latifolia 200C HPUS

Inactive Ingredients

Sucrose, Lactose

Purpose

Relieves neckache from cervical spondylosis

Uses

Relieves neckache from cervical spondylosis

Warnings

If pregnant or breast feeding ask a health professional before use.

Keep out of reach of children. In case of overdose, get medical help or contact a Poison Control Center (1-800-222-1222) right away.

Direction

Adult or child: Take three pills daily. Leaving a gap of 30 minutes after any food or as advised by your physician.

Manufactured by

Paramesh Banerji Life Sciences, LLC.

North Brunswick, NJ 08902, USA.

Tel: +1-732-743-5936

Email: info@pblifesciences.com

Principal Display Panel

NDC: 69152-0033-1

Sponcer 40

Number 33

Homeopathic Medicine

Relieves neckache from cervical spondylosis

96 Pills (Approx.)

Product of USA